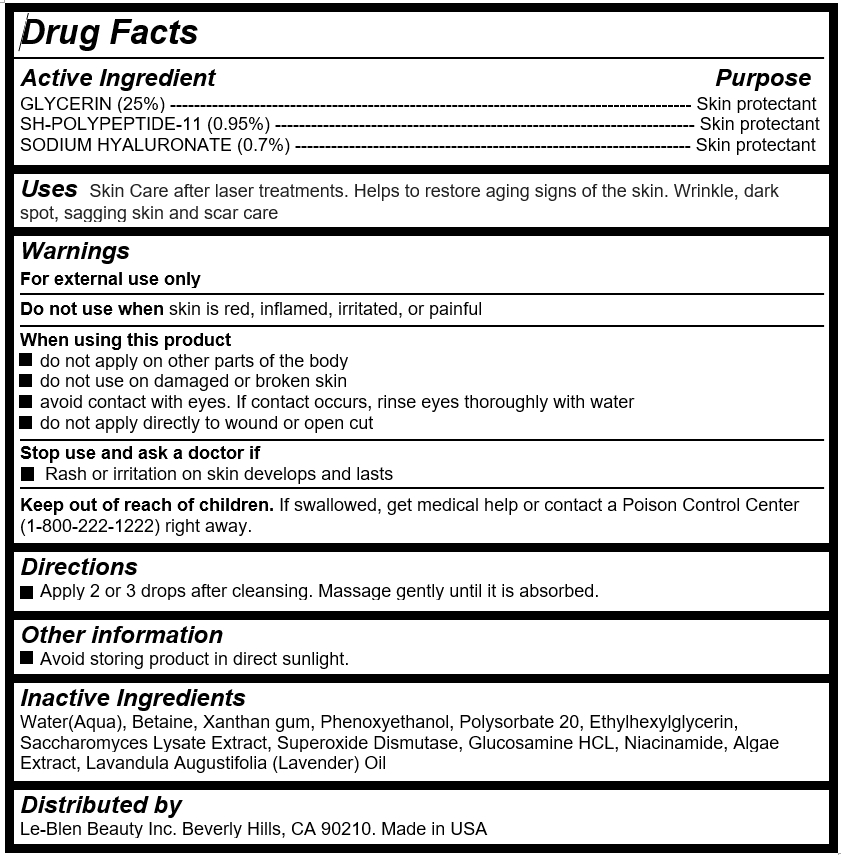 DRUG LABEL: Le-Blen FGF Serum
NDC: 72271-101 | Form: EMULSION
Manufacturer: LeBlen Beauty Inc.
Category: otc | Type: HUMAN OTC DRUG LABEL
Date: 20180425

ACTIVE INGREDIENTS: GLYCERIN 14.18 g/56.7 g; FIBROBLAST GROWTH FACTOR-1 0.54 g/56.7 g; HYALURONATE SODIUM 0.4 g/56.7 g
INACTIVE INGREDIENTS: WATER

Le-Blen FGF Serum

Active Ingredient

GLYCERIN (25%) --------------------------------------------------------------------------------------- Skin protectant

SH-POLYPEPTIDE-11 (0.95%) ---------------------------------------------------------------------- Skin protectant

SODIUM HYALURONATE (0.7%) ------------------------------------------------------------------ Skin protectant

Purpose

Skin protectant

Uses

Skin Care after laser treatments. Helps to restore aging signs of the skin. Wrinkle, dark spot, sagging skin and scar care

Warnings

For external use only

Do not use when skin is red, inflamed, irritated, or painful

When using this product

do not apply on other parts of the body

do not use on damaged or broken skin

avoid contact with eyes. If contact occurs, rinse eyes thoroughly with water

do not apply directly to wound or open cut

Stop use and ask a doctor if

Rash or irritation on skin develops and lasts

Keep out of reach of children

If swallowed, get medical help or contact a Poison Control Center (1-800-222-1222) right away.

Directions

Apply 2 or 3 drops after cleansing. Massage gently until it is absorbed.

Inactive Ingredients

Water(Aqua), Betaine, Xanthan gum, Phenoxyethanol, Polysorbate 20, Ethylhexylglycerin, Saccharomyces Lysate Extract, Superoxide Dismutase, Glucosamine HCL, Niacinamide, Algae Extract, Lavandula Augustifolia (Lavender) Oil